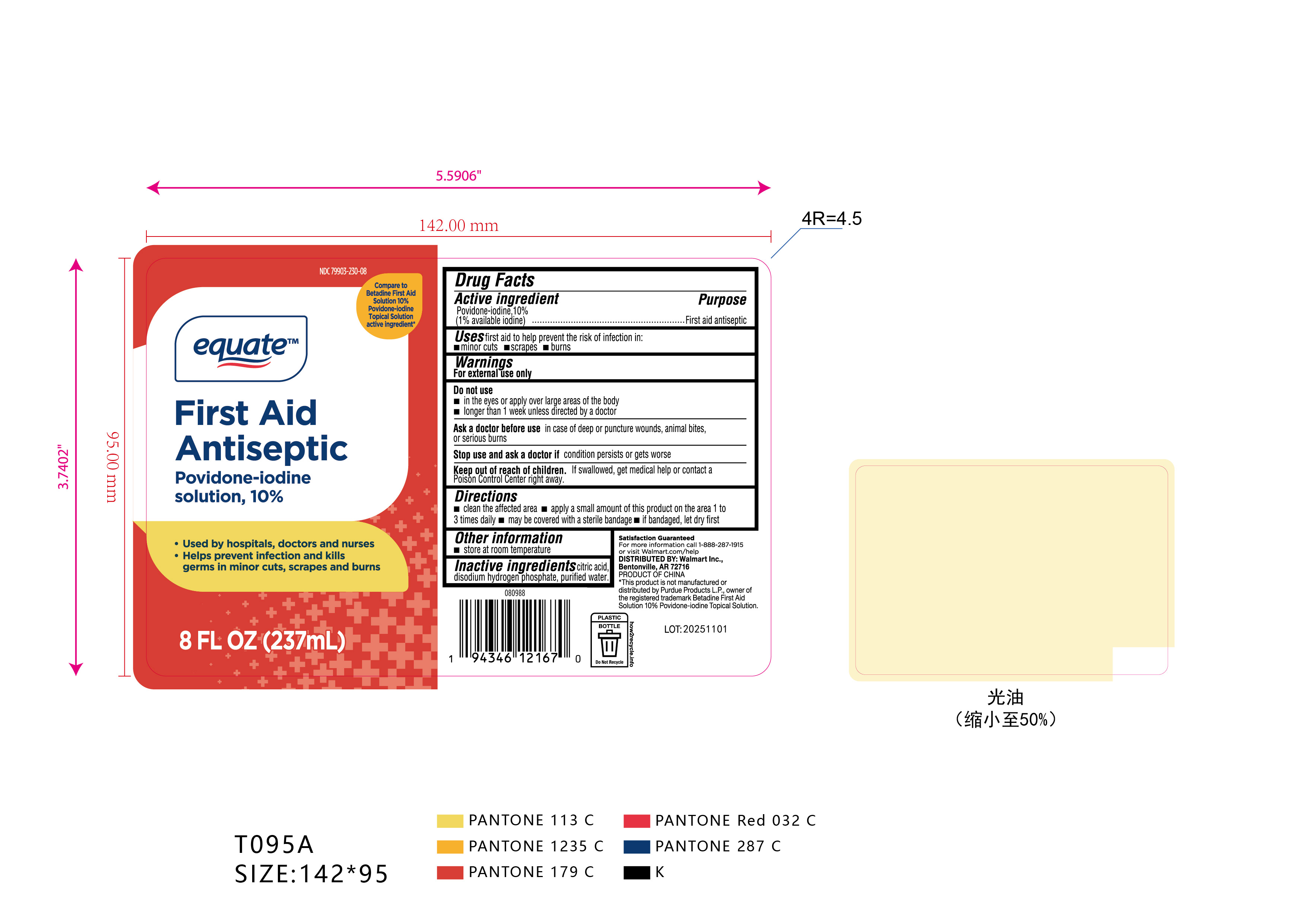 DRUG LABEL: equate First Aid Antiseptic
NDC: 79903-230 | Form: SOLUTION
Manufacturer: Walmart Inc.
Category: otc | Type: HUMAN OTC DRUG LABEL
Date: 20251014

ACTIVE INGREDIENTS: POVIDONE-IODINE 1 g/100 mL
INACTIVE INGREDIENTS: WATER; CITRIC ACID MONOHYDRATE; SODIUM PHOSPHATE DIBASIC DIHYDRATE

Walmart 79903-230-08

Active Ingredient: Povidone-Iodine USP (10%)

(1% available Iodine)

Purpose: First Aid Antiseptic

Use:

First aid antiseptic to help prevent the risk of infection in minor cuts, scrapes and burns.

Warnings:

For external use only

Do not use

- to the eyes or over large areas of the body
- longer than a week unless directed by a doctor

Ask a doctor before use in case of deep or puncture wounds, animal bites, or serious burns

Stop use and ask a doctor if condition persists or gets worse

Keep out of reach of children. If swallowed, get medical help or consult a poison control center right away

Directions

- clean the affacted area,
- apply a small anount of the product to the area 1-3 times daily.
- maybe covered with a sterile bandage.
- if bandaged, let dry first.

Other information

- Store between 15-30C (59-86F)

Inactive Ingredient

Citric acid, disodium hydrogen phosphate, purified water